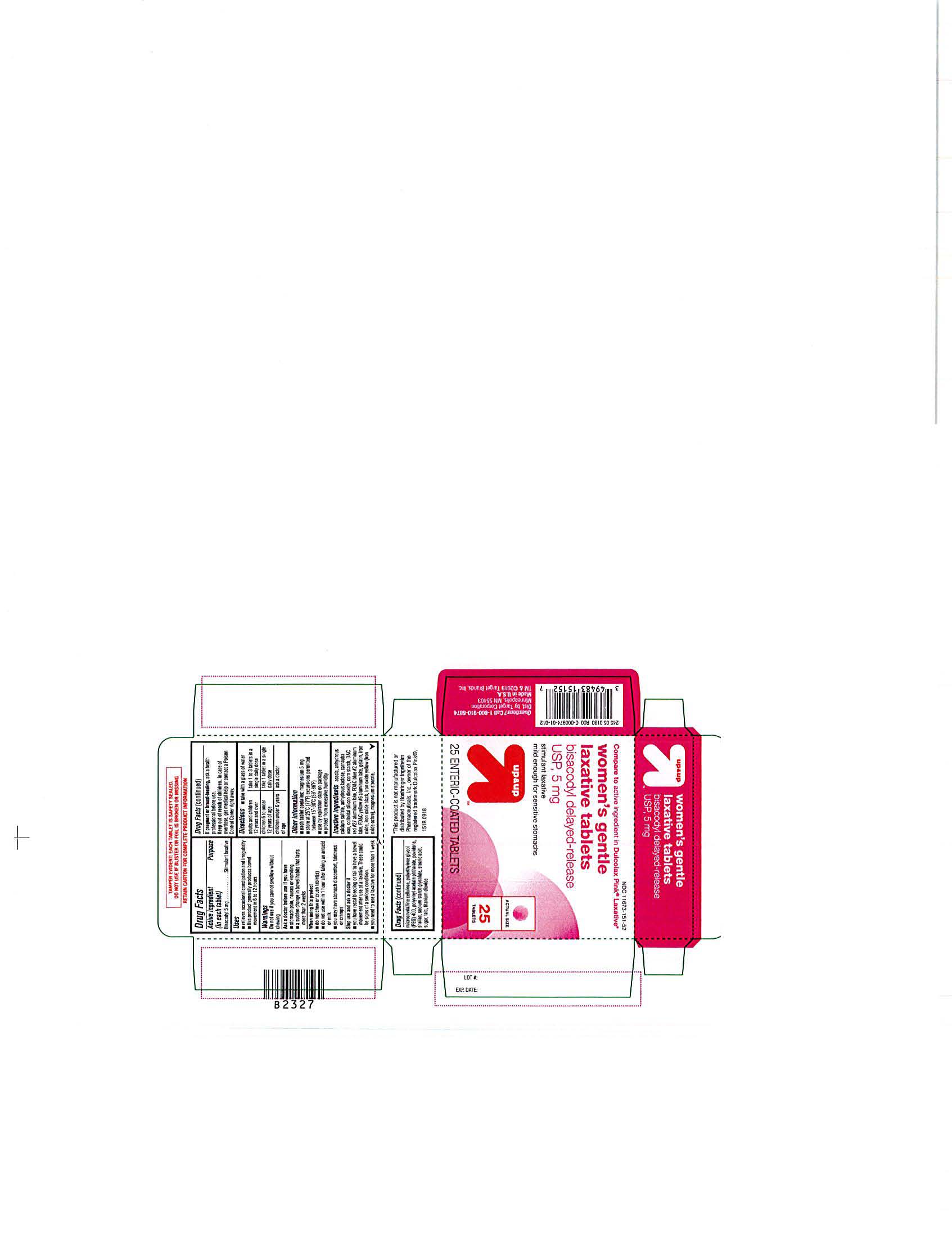 DRUG LABEL: WOMENS GENTLE LAXATIVE
NDC: 11673-151 | Form: TABLET
Manufacturer: TARGET CORPORATION
Category: otc | Type: HUMAN OTC DRUG LABEL
Date: 20190416

ACTIVE INGREDIENTS: BISACODYL 5 mg/1 1
INACTIVE INGREDIENTS: FD&C BLUE NO. 2; FERRIC OXIDE YELLOW; MAGNESIUM STEARATE; POLYETHYLENE GLYCOL 400; POVIDONE; SODIUM STARCH GLYCOLATE TYPE A CORN; POLYVINYL ACETATE PHTHALATE; RAW SUGAR; ACACIA; FERROSOFERRIC OXIDE; STEARIC ACID; ANHYDROUS LACTOSE; CARNAUBA WAX; STARCH, CORN; D&C RED NO. 27; FD&C YELLOW NO. 6; GELATIN; FERROUS OXIDE; CALCIUM SULFATE ANHYDROUS; SILICON DIOXIDE; MICROCRYSTALLINE CELLULOSE; SHELLAC; TALC; TITANIUM DIOXIDE

TARGET 151R 25 COUNT BLISTERS

ACTIVE INGREDIENT

In each tablet: Bisacodyl 5mg

INACTIVE INGREDIENTS

Acacia, Anhydrous Calcium Sulfate, Anhydrous Lactose, Carnauba Wax, Colloidal Silicon Dioxide, Corn Starch, D&C Red #27 Aluminum Lake, FD&C Blue #2 Aluminum Lake, FD&C Yellow #6 Aluminum Lake, Gelatin, Iron Oxide, Iron Oxide Black, Iron Oxide Yellow (Iron Oxide Ochre), Magnesium Stearate,Microcrystalline Cellulose, Polyethylene Glycol (PEG) 400, Polyvinyl Acetate Phthalate, Povidone,Shellac, Sodium Starch Glycolate, Stearic Acid, Sugar, Talc, Titanium Dioxide

PURPOSE

Stimulant Laxative

Keep out of Reach of Children: In case of overdose, get medical help or contact a Poison Control Center right away.

INDICATIONS AND USAGE

Temporarily relieves occasional constipation and irregularity

WARNINGS

Warning: Do not use if you cannot swallow without chewing.

Ask a doctor before use if you have: stomach pain, nausea or vomiting; A sudden change in bowel habits that lasts more than two weeks.

When using this product: Do not chew or crush tablet(s); Do not use within 1 hour after taking an antacid or milk; Do not use this product if you have stomack discomfort, faintness or cramps.

DOSAGE AND ADMINISTRATION

adults and children 12 years and over: take 1 to 3 tablets (usually 2A) daily, or as directed by a doctor
children 6 to under 12 years: take 1 tablet daily, or as directed by a doctor
children under 6 year ask a doctor